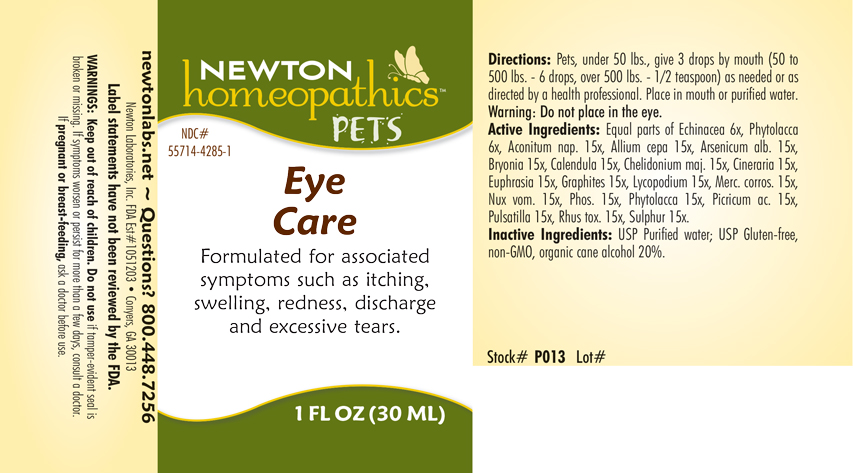 DRUG LABEL: Eye Care
NDC: 55714-4285 | Form: LIQUID
Manufacturer: Newton Laboratories, Inc.
Category: homeopathic | Type: OTC ANIMAL DRUG LABEL
Date: 20180228

ACTIVE INGREDIENTS: Aconitum Napellus 15 [hp_X]/1 mL; Onion 15 [hp_X]/1 mL; Arsenic Trioxide 15 [hp_X]/1 mL; Bryonia Alba Root 15 [hp_X]/1 mL; Calendula Officinalis Flowering Top 15 [hp_X]/1 mL; Chelidonium Majus 15 [hp_X]/1 mL; Jacobaea Maritima 15 [hp_X]/1 mL; Euphrasia Stricta 15 [hp_X]/1 mL; Graphite 15 [hp_X]/1 mL; Lycopodium Clavatum Spore 15 [hp_X]/1 mL; Mercuric Chloride 15 [hp_X]/1 mL; Strychnos Nux-vomica Seed 15 [hp_X]/1 mL; Phosphorus 15 [hp_X]/1 mL; Phytolacca Americana Root 15 [hp_X]/1 mL; Picric Acid 15 [hp_X]/1 mL; Anemone Pulsatilla 15 [hp_X]/1 mL; Toxicodendron Pubescens Leaf 15 [hp_X]/1 mL; Sulfur 15 [hp_X]/1 mL; Echinacea, Unspecified 6 [hp_X]/1 mL
INACTIVE INGREDIENTS: Alcohol

Eye Care

INDICATIONS & USAGE SECTION

Formulated for associated symptoms such as itching, swelling, redness, discharge and excessive tears.

DOSAGE & ADMINISTRATION SECTION

Directions: Pets, under 50 lbs., give 3 drops by mouth (50 to 500 lbs. - 6 drops, over 500 lbs. - 1/2 teaspoon) as needed or as directed by a health professional. Place in mouth or purified water. Warning: Do not place in the eye.

OTC - ACTIVE INGREDIENT SECTION

Equal parts of Echinacea 6x, Phytolacca 6x, Aconitum nap. 15x, Allium cepa 15x, Arsenicum alb. 15x, Bryonia 15x, Calendula 15x, Chelidonium majus 15x, Cineraria 15x, Euphrasia 15x, Graphites 15x, Lycopodium 15x, Merc. corros. 15x, Nux vom. 15x, Phos. 15x, Phytolacca 15x, Picricum ac. 15x, Pulsatilla 15x, Rhus tox. 15x, Sulphur 15x.

OTC - PURPOSE SECTION

Formulated for associated symptoms such as itching, swelling, redness, discharge and excessive tears.

INACTIVE INGREDIENT SECTION

USP Purified Water; USP Gluten-free, non-GMO, organic cane alcohol 20%.

QUESTIONS SECTION

newtonlabs.net ~ Questions? 800.448.7256 Newton Laboratories, Inc. FDA Est # 1051203 - Conyers, GA 30013

WARNINGS SECTION

Warning: Keep out of reach of children. Do not use if tamper-evident seal is broken or missing. If symptoms worsen or persist for more than a few days, consult a doctor.
If pregnant or breast-feeding, ask a doctor before use.

OTC - PREGNANCY OR BREAST FEEDING SECTION

If pregnant or breast-feeding, ask a doctor before use.

OTC - KEEP OUT OF REACH OF CHILDREN SECTION

Keep out of reach of children.